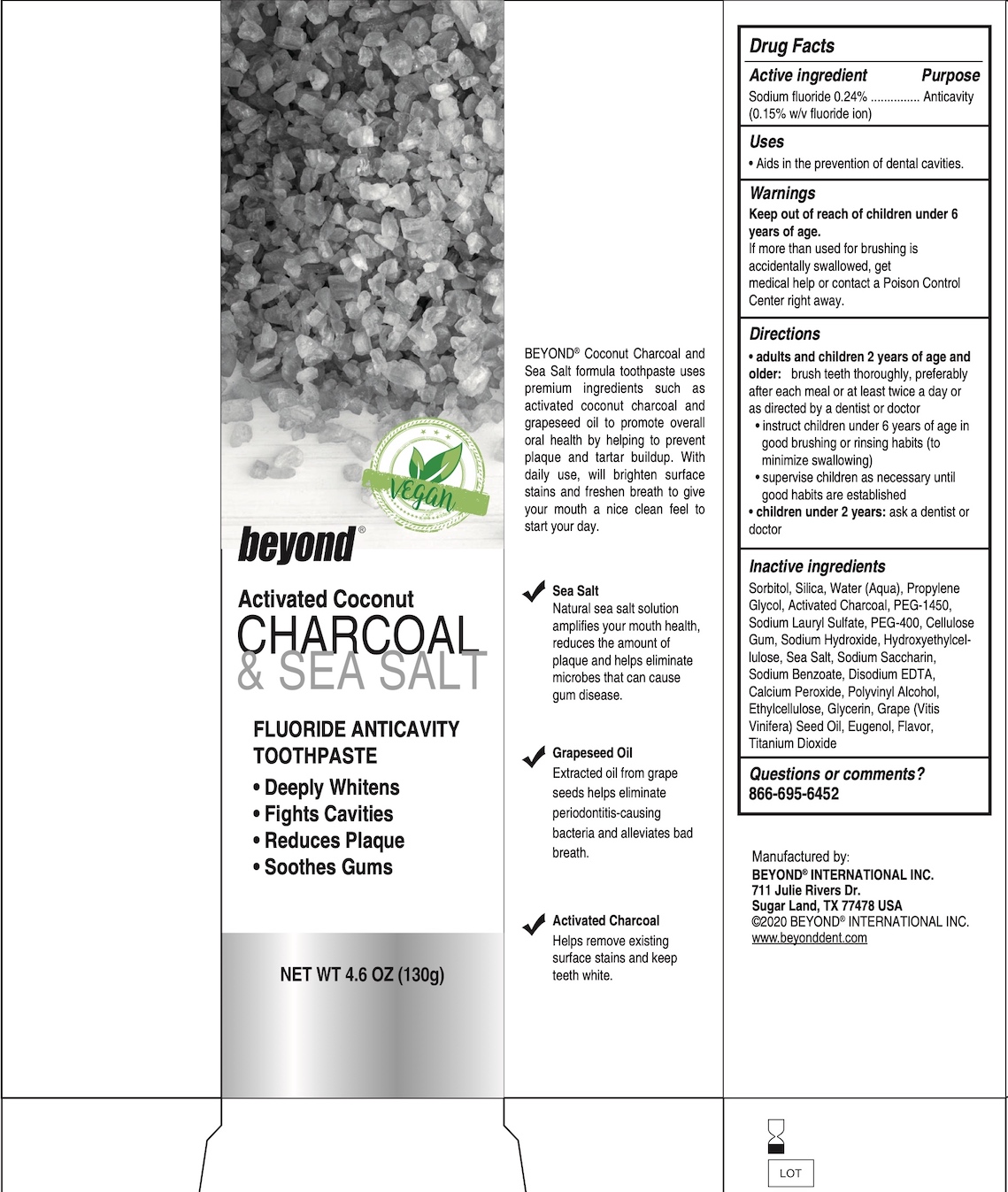 DRUG LABEL: Beyond Activated Coconut Charcoal and Sea Salt
NDC: 42199-008 | Form: PASTE, DENTIFRICE
Manufacturer: Beyond International Inc
Category: otc | Type: HUMAN OTC DRUG LABEL
Date: 20231128

ACTIVE INGREDIENTS: SODIUM FLUORIDE 0.24 g/100 g
INACTIVE INGREDIENTS: CALCIUM PEROXIDE; GRAPE SEED OIL; EUGENOL; CARBOXYMETHYLCELLULOSE SODIUM, UNSPECIFIED; EDETATE DISODIUM ANHYDROUS; ETHYLCELLULOSES; GLYCERIN; HYDRATED SILICA; WATER; SORBITOL; PROPYLENE GLYCOL; ACTIVATED CHARCOAL; POLYETHYLENE GLYCOL 400; HYDROXYETHYL CELLULOSE (5000 MPA.S AT 1%); POLYETHYLENE GLYCOL 1450; SODIUM BENZOATE; TITANIUM DIOXIDE; SACCHARIN SODIUM; SODIUM LAURYL SULFATE; SEA SALT; SODIUM HYDROXIDE; POLYVINYL ALCOHOL, UNSPECIFIED

Charcoal and Sea Salt Toothpaste

Drug Facts

Active ingredient

Sodium fluoride 0.24% (0.15% w/v fluoride ion)

Purpose

Anticavity

Uses

- Aids in prevention of dental cavities.

Warnings

Keep out of reach of children under 6 years of age.

If more than used for brushing is accidentally swallowed, get medical help or contact a Poison Control Center right away.

Directions

- adults and children 2 years of age and older: brush teeth thoroughly, preferably after each meal or at least twice a day, or as directed by a dentist or doctor.
- instruct children under 6 years of age in good brushing or rinsing habits (to minimize swallowing)
- supervise children as necessary until good habits are established
- children under 2 years: ask a dentist or doctor

INACTIVE INGREDIENT

Inactive ingredients Sorbitol, Silica, Water (Aqua), Propylene Glycol, Activated Charcoal, PEG-1450, Sodium Lauryl Sulfate, PEG-400, Cellulose Gum, Sodium Hydroxide, Hydroxyethylellulose, Sea Salt, Sodium Saccharin, Sodium Benzoate, Disodium EDTA, Calcium Peroxide, Polyvinyl Alcohol, Ethylcellulose, Glycerin, Grape (Vitis Vinifera) Seed Oil, Eugenol, Flavor, Titanium Dioxide

Questions or comments? 866-695-6452

Manufactured by:

BEYOND® INTERNATIONAL INC.

711 Julie Rivers Dr.

Sugar Land, TX 77478 USA

©2020 BEYOND® INTERNATIONAL INC.

www.beyonddent.com

PACKAGE LABEL

Vegan

beyond®

Activated Coconut CHARCOAL & SEA SALT

FLUORIDE ANTICAVITY TOOTHPASTE

- Deeply Whitens
- Fights Cavities
- Reduces Plaque
- Soothes Gums

NET WT. 4.6 OZ (130g)